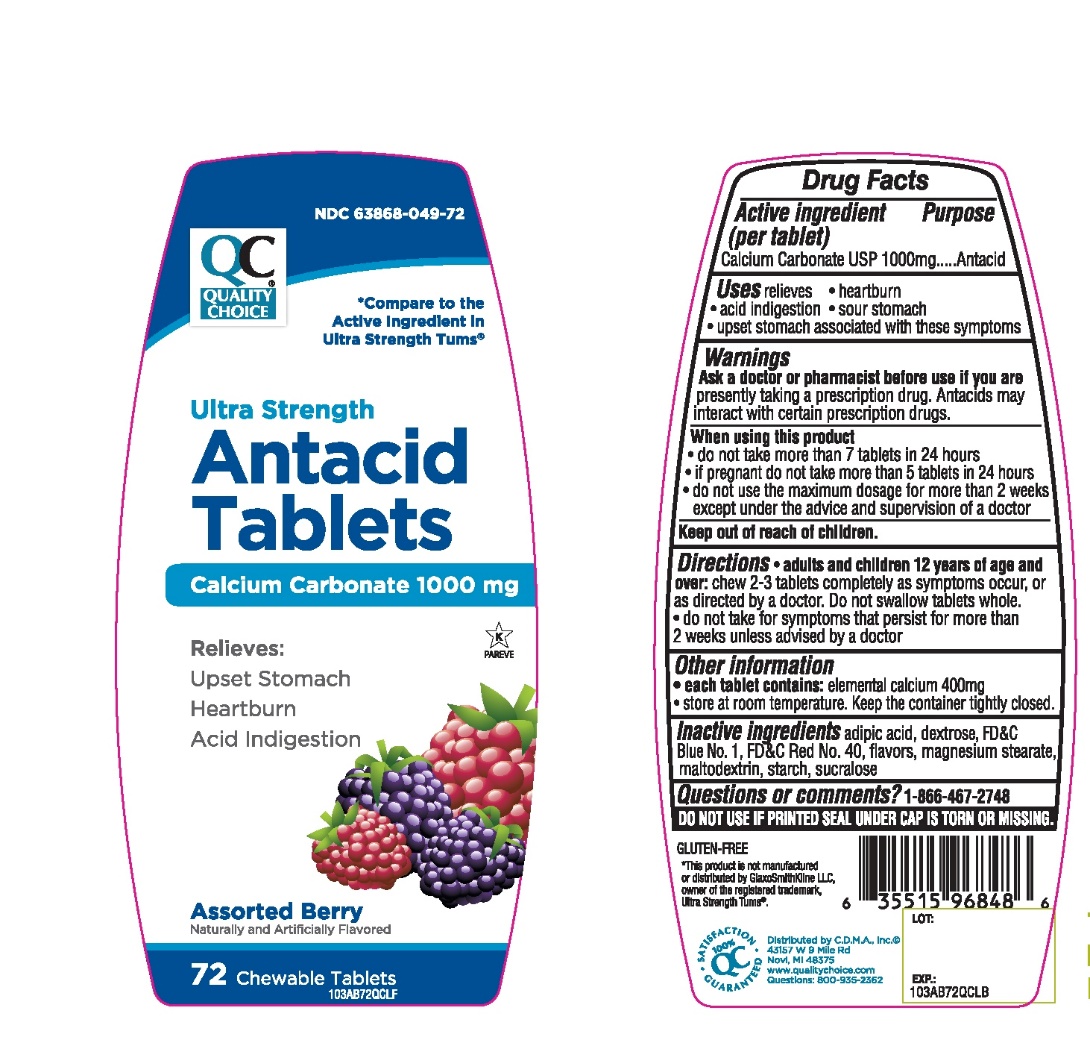 DRUG LABEL: QC Antacid Calcium

NDC: 63868-049 | Form: TABLET, CHEWABLE
Manufacturer: CHAIN DRUG MARKETING ASSOCIATION INC.
Category: otc | Type: HUMAN OTC DRUG LABEL
Date: 20251203

ACTIVE INGREDIENTS: CALCIUM CARBONATE 1000 mg/1 1
INACTIVE INGREDIENTS: ADIPIC ACID; FD&C BLUE NO. 1; DEXTROSE, UNSPECIFIED FORM; MAGNESIUM STEARATE; MALTODEXTRIN; FD&C RED NO. 40; STARCH, CORN; SUCRALOSE

Ultra Strength Assorted Berry Antacid Calcium Supplement Drug Facts

Active ingredient (per tablet)

Calcium Carbonate USP 1000mg

Purpose

Antacid

Uses

relieves

- heartburn
- acid indigestion
- sour stomach
- upset stomach associated with these symptoms

Ask a doctor or pharmacist before use if you are

taking a prescription drug. Antacids may interact with certain prescription drugs.

When using this product

- do not take more than 7 tablets in 24 hours
- do not use the maximum dosage for more than 2 weeks.

Directions

- chew 2-3 tablets as symptoms occur, or as directed by a doctor

Other Information

- Store below 30°C (86°F).
- Keep the container tightly closed
- For calcium and magnesium content see Supplement Facts.

Safety sealed: Do not use if printed seal under cap is torn or missing.

Inactive ingredients

adipic acid, blue 1 lake, dextrose, flavor, flavors, magnesium stearate, maltodextrin, red 40 lake, starch, sucralose.

Package/Label Principal Display Panel

QUALITY CHOICE®

NDC# 63868-049-72

Compare To Tums®Ultra Strength active ingredient*

ULTRA STRENGTH

Antacid Tablets

Antacid Calcium Supplement

CALCIUM CARBONATE 1000 mg

Relieves:

- Upset Stomach
- Heartburn
- Acid Indigestion

Assorted Berry

GLUTEN FREE

72 CHEWABLE TABLETS

K PAREVE

QC SATISFACTION GURANTEED

©Distributed by: C.D.M.A., Inc.

43157 W Nine Mile

Novi, MI 48376-0995

www.qualitychoice.com

Questions: 248-449-9300

*This product is not manufactured or distributed by GlaxoSmithKline, the distributor of Tums®.